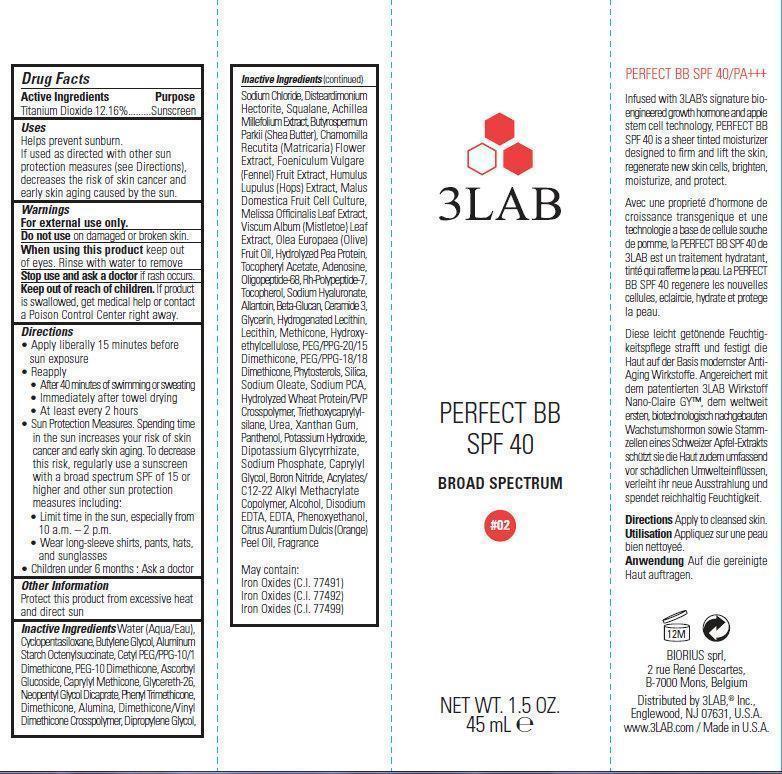 DRUG LABEL: 3LAB PERFECT BB SPF 40 Broad Spectrum 02
NDC: 76159-002 | Form: CREAM
Manufacturer: 3LAB, Inc
Category: otc | Type: HUMAN OTC DRUG LABEL
Date: 20231212

ACTIVE INGREDIENTS: TITANIUM DIOXIDE 121.6 mg/1 mL
INACTIVE INGREDIENTS: WATER; CYCLOMETHICONE 5; BUTYLENE GLYCOL; ALUMINUM STARCH OCTENYLSUCCINATE; ASCORBYL GLUCOSIDE; CAPRYLYL TRISILOXANE; GLYCERETH-26; NEOPENTYL GLYCOL DICAPRATE; PHENYL TRIMETHICONE; DIMETHICONE; ALUMINUM OXIDE; DIPROPYLENE GLYCOL; SODIUM CHLORIDE; SQUALANE; FENNEL SEED; ACHILLEA MILLEFOLIUM; SHEA BUTTER; CHAMOMILE; HOPS; MELISSA OFFICINALIS LEAF; VISCUM ALBUM FRUITING TOP; OLIVE OIL; .ALPHA.-TOCOPHEROL ACETATE; ADENOSINE; TOCOPHEROL; HYALURONATE SODIUM; ALLANTOIN; CERAMIDE 3; GLYCERIN; PEG/PPG-20/15 DIMETHICONE; PEG/PPG-18/18 DIMETHICONE; SILICON DIOXIDE; SODIUM OLEATE; SODIUM PYRROLIDONE CARBOXYLATE; TRIETHOXYCAPRYLYLSILANE; UREA; XANTHAN GUM; PANTHENOL; POTASSIUM HYDROXIDE; GLYCYRRHIZINATE DIPOTASSIUM; SODIUM PHOSPHATE; CAPRYLYL GLYCOL; BORON NITRIDE; ALCOHOL; EDETATE DISODIUM; EDETIC ACID; PHENOXYETHANOL; ORANGE OIL; FERRIC OXIDE RED; FERRIC OXIDE YELLOW; FERROSOFERRIC OXIDE

3LAB PERFECT BB SPF 40 Broad Spectrum 02

Active Ingredients

Titanium Dioxide 12.16%

Purpose

Sunscreen

Uses

Helps prevent sunburn. If used as directed with other sun protection measures (see Directions), decreases the risk of skin cancer and early skin aging caused by the sun.

Warnings

For external use only.

Do not use

on damaged or broken skin.

When using this product

keep out of eyes. Rinse with water to remove

Stop use and ask a doctor

if rash occurs.

Keep out of reach of children.

If product is swallowed, get medical help or contact a Poison Control Center right away.

Directions

• Apply liberally 15 minutes before sun exposure • Reapply • After 40 minutes of swimming or sweating • Immediately after towel drying • At least every 2 hours • Sun Protection Measures. Spending time in the sun increases your risk of skin cancer and early skin aging. To decrease this risk, regularly use a sunscreen with a broad spectrum SPF of 15 or higher and other sun protection measures including: • Limit time in the sun, especially from 10 a.m. – 2 p.m. • Wear long-sleeve shirts, pants, hats, and sunglasses • Children under 6 months : Ask a doctor

Other Information

Protect this product from excessive heat and direct sun

Inactive Ingredients

Water (Aqua/Eau),Cyclopentasiloxane, Butylene Glycol, Aluminum Starch Octenylsuccinate, Cetyl PEG/PPG-10/1Dimethicone, PEG-10 Dimethicone, Ascorbyl Glucoside, Caprylyl Methicone, Glycereth-26, Neopentyl Glycol Dicaprate, Phenyl Trimethicone, Dimethicone, Alumina, Dimethicone/Vinyl Dimethicone Crosspolymer, Dipropylene Glycol,Sodium Chloride, Disteardimonium Hectorite, Squalane, Achillea Millefolium Extract, Butyrospermum Parkii (Shea Butter), Chamomilla Recutita (Matricaria) Flower Extract, Foeniculum Vulgare (Fennel) Fruit Extract, Humulus Lupulus (Hops) Extract, Malus Domestica Fruit Cell Culture, Melissa Officinalis Leaf Extract, Viscum Album (Mistletoe) Leaf Extract, Olea Europaea (Olive) Fruit Oil, Hydrolyzed Pea Protein, Tocopheryl Acetate, Adenosine, Oligopeptide-68, Rh-Polypeptide-7, Tocopherol, Sodium Hyaluronate, Allantoin, Beta-Glucan, Ceramide 3, Glycerin, Hydrogenated Lecithin, Lecithin, Methicone, Hydroxyethylcellulose, PEG/PPG-20/15 Dimethicone, PEG/PPG-18/18 Dimethicone, Phytosterols, Silica, Sodium Oleate, Sodium PCA, Hydrolyzed Wheat Protein/PVP Crosspolymer, Triethoxycaprylylsilane, Urea, Xanthan Gum, Panthenol, Potassium Hydroxide, Dipotassium Glycyrrhizate, Sodium Phosphate, Caprylyl Glycol, Boron Nitride, Acrylates/C12-22 Alkyl Methacrylate Copolymer, Alcohol, Disodium EDTA, EDTA, Phenoxyethanol, Citrus Aurantium Dulcis (Orange) Peel Oil, Fragrance May contain: Iron Oxides (C.I. 77491) Iron Oxides (C.I. 77492) Iron Oxides (C.I. 77499)

PERFECT BB SPF 40/PA+++

Infused with 3LAB’s signature bioengineered growth hormone and apple stem cell technology, PERFECT BB SPF 40 is a sheer tinted moisturizer designed to firm and lift the skin, regenerate new skin cells, brighten, moisturize, and protect.

Apply to cleansed skin. Directions

BIORIUS sprl,2 rue René Descartes,B-7000 Mons, Belgium Distributed by 3LAB,® Inc., Englewood, NJ 07631, U.S.A. www.3LAB.com / Made in U.S.A.

PACKAGE LABEL

3LAB PERFECT BB SPF 40 BROAD SPECTRUM #02 NET WT. 1.5 OZ. 45 mL e